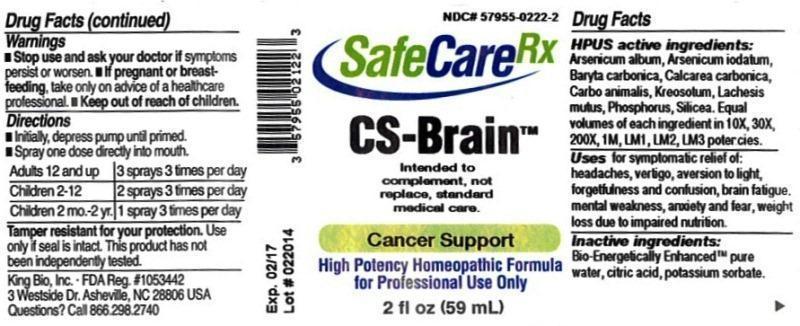 DRUG LABEL: CS Brain
NDC: 57955-0222 | Form: LIQUID
Manufacturer: King Bio Inc.
Category: homeopathic | Type: HUMAN OTC DRUG LABEL
Date: 20140331

ACTIVE INGREDIENTS: ARSENIC TRIOXIDE 10 [hp_X]/59 mL; ARSENIC TRIIODIDE 10 [hp_X]/59 mL; BARIUM CARBONATE 10 [hp_X]/59 mL; OYSTER SHELL CALCIUM CARBONATE, CRUDE 10 [hp_X]/59 mL; CARBO ANIMALIS 10 [hp_X]/59 mL; WOOD CREOSOTE 10 [hp_X]/59 mL; LACHESIS MUTA VENOM 10 [hp_X]/59 mL; PHOSPHORUS 10 [hp_X]/59 mL; SILICON DIOXIDE 10 [hp_X]/59 mL
INACTIVE INGREDIENTS: WATER; CITRIC ACID MONOHYDRATE; POTASSIUM SORBATE

CS Brain

ACTIVE INGREDIENT

HPUS active ingredients: Arsenicum album, Arsenicum iodatum, Baryta carbonica, Calcarea carbonica, Carbo animalis, Kreosotum, Lachesis mutus, Phosphorus, Silicea. Equal volumes of each ingredient in 10X, 30X, 200X, 1M, LM1, LM2, LM3 potencies.

PURPOSE

Uses for symptomatic relief of: headaches, vertigo, aversion to light, forgetfulness and confusion, brain fatigue, mental weakness, anxiety and fear, weight loss due to impaired nutrition.

Inactive Ingredients:

Bio-Energetically Enhanced™ pure water base, Citric acid and Potassium sorbate.

Warning

- Stop use and ask a doctor if symptoms persist or worsen.
- If pregnant or breast-feeding, take only on advice of a healthcare professional.

- Keep out of reach of children.

Directions

- Initially, depress pump until primed.
- Spray one dose directly into mouth.
- Adults 12 and up: 3 sprays 3 times per day.
- Children 2-12: 2 sprays 3 times per day.
- Children 2 mo.-2 yr: 1 spray 3 times per day

Other Information:

- Tamper resistant for your protection.
- Use only if seal is intact.
- This product has not been independently tested.
- Intended to complement, no replace, standard medical care.

INDICATIONS AND USAGE

Uses for symptomatic relief of:

- headaches
- vertigo
- aversion to light
- forgetfulness and confusion
- brain fatigue
- mental weakness
- anxiety and fear
- weight loss due to impaired nutrition.